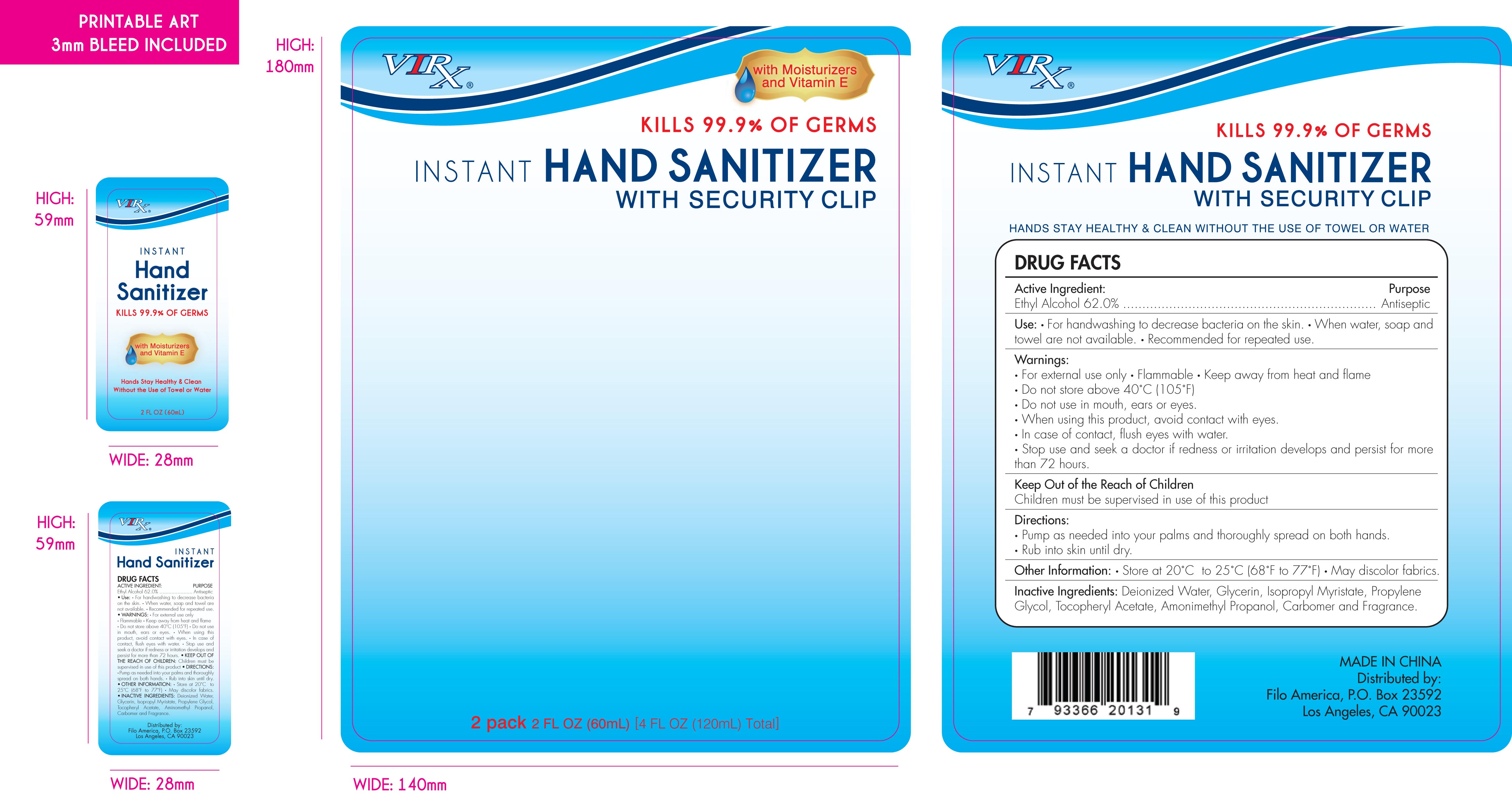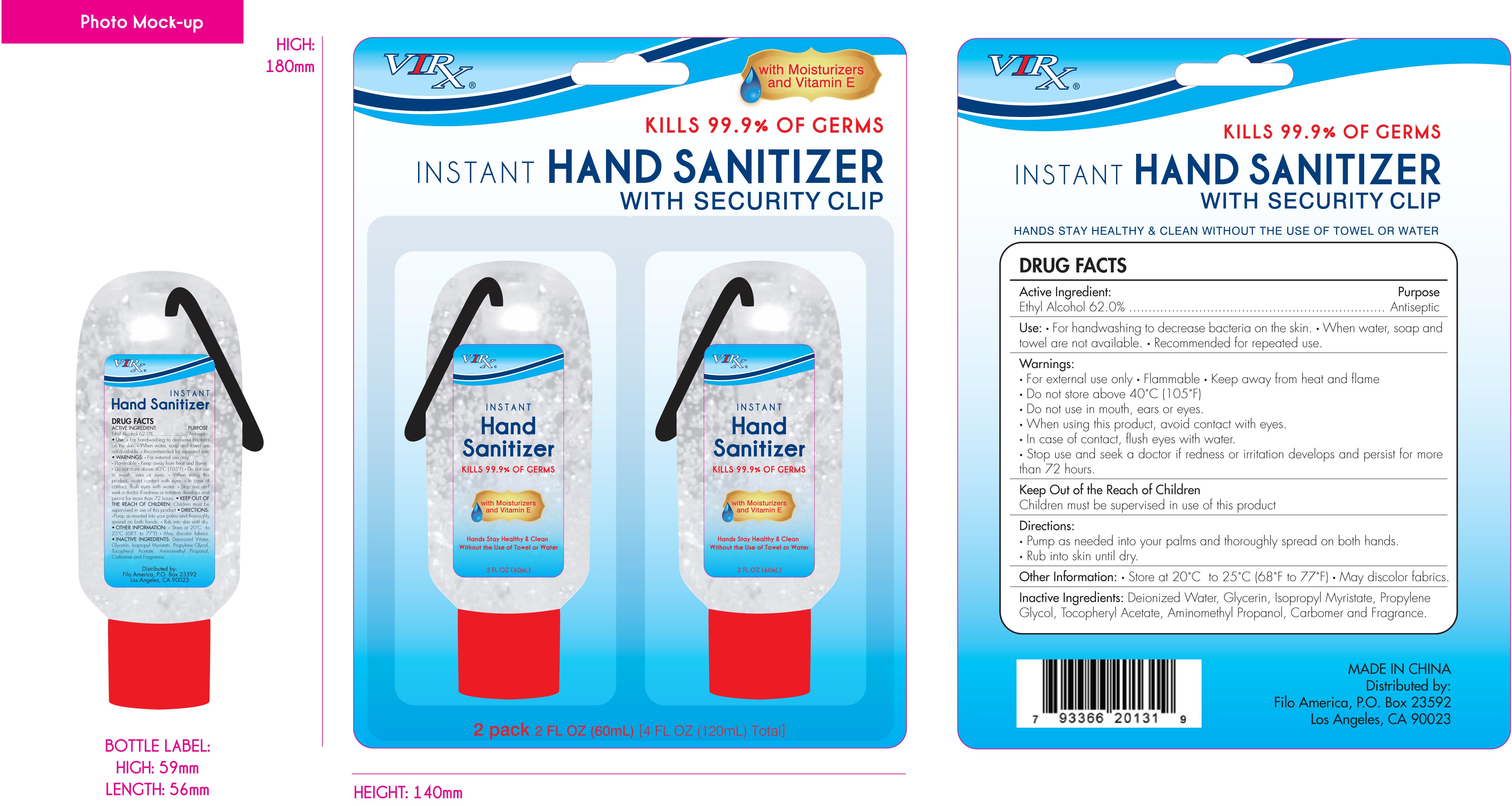 DRUG LABEL: Virx
NDC: 29860-203 | Form: GEL
Manufacturer: Ningbo United Group Co. Ltd.
Category: otc | Type: HUMAN OTC DRUG LABEL
Date: 20100225

ACTIVE INGREDIENTS: Alcohol  74.40 mL/120 mL
INACTIVE INGREDIENTS: Water; Glycerin; Isopropyl Myristate; Propylene Glycol; ALPHA-TOCOPHEROL; Carbomer 934

Virx Hand Sanitizer Drug Facts

Active Ingredient: Purpose
Ethyl Alcohol 62%...........................................................................Antiseptic

PURPOSE

Use * for handwashing to decrease bacteria on the skin * When water, soap and towel are not available * Recommended for repeated use.

Warnings:
* For external use only * Flammable * Keep away from heat and flame
* Do not store above 40 degrees Celcius (105 degrees Farenheit)
* Do not use in mouth, ears or eyes.
* When using this product, avoid contact with eyes.
* In case of contact, flush eyes with water.
* Stop use and seek a doctor if redness or irritation develops and persist for more than 72 hours.

KEEP OUT OF REACH OF CHILDREN

Children must be supervised in use of this product.

INDICATIONS AND USAGE

* Pump as needed into your palms and thoroughly spread on both hands.
* Rub into skin until dry.

Other Information: Store at 20 degrees to 25 degrees Celcius (68-77 degrees Farenheit). May discolor fabrics.

INACTIVE INGREDIENT

Deionized Water, Glycerin, Isopropyl Myristate, Propylene Glycol, Tocopheryl Acetate, Aminomethyl Propanol, Carbomer and Fragrance.

PACKAGE LABEL

MM1
MM2